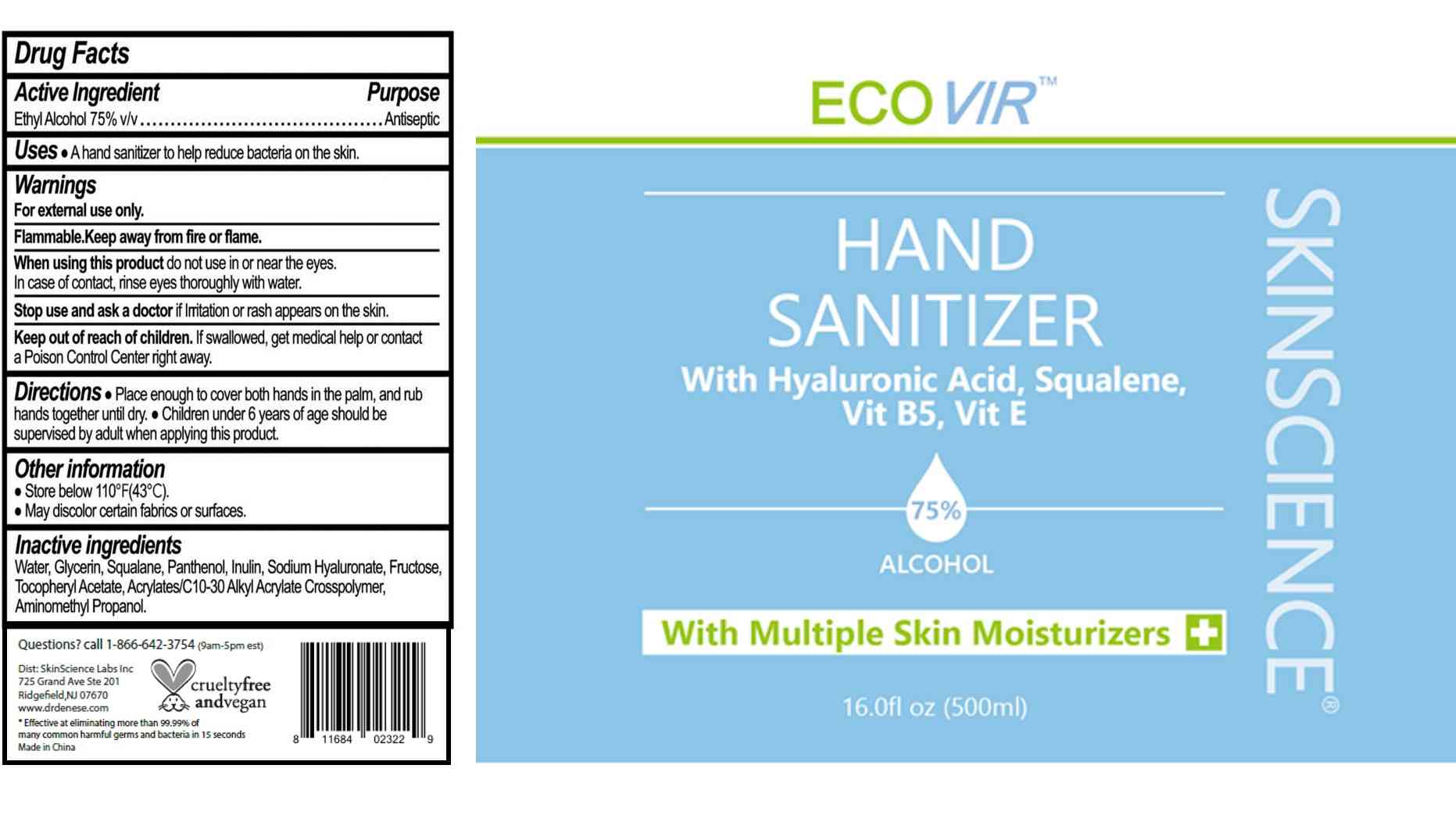 DRUG LABEL: EcoVir Hand Sanitizer
NDC: 66171-200 | Form: LIQUID
Manufacturer: SkinScience Labs, Inc.
Category: otc | Type: HUMAN OTC DRUG LABEL
Date: 20200514

ACTIVE INGREDIENTS: ALCOHOL 75 mL/100 mL
INACTIVE INGREDIENTS: WATER

EcoVir Hand Sanitizer

Active Ingredient

Ethyl Alcohol 75% v/v

Purpose

Antiseptic

Uses

A hand sanitizer to help reduce bacteria on the skin.

Warnings

For external use only.

Flammable. Keep away from fire or flame.

When using this product

do not use in or near the eyes.

In case of contact, rinse eyes thoroughly with water.

Stop use and ask a doctor

if irritation or rash appears on the skin.

Keep out of reach of children.

If swallowed, get medical help or contact a Poison Control Center right away.

Directions

Place enough to cover both hands in the palm, and rub hands together until dry.

Children under 6 years of age should be supervised by adult when applying this product.

Other Information

Store below 110degF (43degC)

Inactive Ingredients

Water, Glycerin, Squalane, Panthenol, Inulin, Sodium Hyaluronate, Fructose, Tocopheryl Acetate, Acrylates/C10-30 Alkyl Acrylate Crosspolymer, Aminomethyl Propanol

Questions?

Call 1-866-642-3754 (9am-5pm est)

Directions:

Place enough to cover both hands in the palm, and rub hands together until dry.

Children under 6 years of age should be supervised by adult when applying this product.